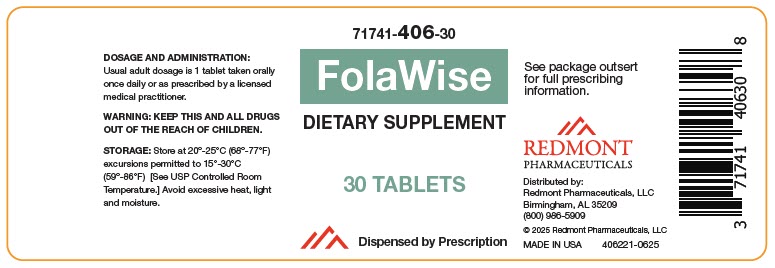 DRUG LABEL: FolaWise
NDC: 71741-406 | Form: TABLET
Manufacturer: Redmont Pharmaceuticals, LLC
Category: other | Type: DIETARY SUPPLEMENT
Date: 20250623

ACTIVE INGREDIENTS: Beta Carotene 300 ug/1 1; Ascorbic Acid 90 mg/1 1; Cholecalciferol 20 ug/1 1; .ALPHA.-TOCOPHEROL ACETATE 4.5 mg/1 1; THIAMINE MONONITRATE 1.2 mg/1 1; Riboflavin 1.3 mg/1 1; PYRIDOXINE HYDROCHLORIDE 26 mg/1 1; Folic Acid 0.4 mg/1 1; LEVOMEFOLATE CALCIUM 0.6 mg/1 1; Cyanocobalamin 0.013 mg/1 1
INACTIVE INGREDIENTS: HYDROXYPROPYL CELLULOSE, UNSPECIFIED; Croscarmellose Sodium; Stearic Acid; Silicon Dioxide; MAGNESIUM PALMITOSTEARATE; Titanium Dioxide; POLYETHYLENE GLYCOL, UNSPECIFIED

FolaWise

STATEMENT OF IDENTITY

71741-406-30
Multivitamin Dietary Supplement
Dispensed by Prescription

DESCRIPTION

FolaWise is a prescription multivitamin dietary supplement.

STATEMENT OF IDENTITY

Supplement Facts
Serving size: 1 Tablet
Amount per Serving: | %Daily Value
Vitamin A (as Beta-Carotene) | 300 mcg RAE | 33%
Vitamin C (as Ascorbic Acid) | 90 mg | 100%
Vitamin D3 (as Cholecalciferol) | 20 mcg | 100%
Vitamin E (as dl-Alpha Tocopherol Acetate) | 4.5 mg (10 IU) | 30%
Thiamin | 1.2 mg | 100%
Riboflavin | 1.3 mg | 100%
Vitamin B6 (as Pyridoxine HCl) | 26 mg | 1529%
Folate | 1.67 mg DFE | 418%
(from Folic Acid) | 0.67 mg DFE
(as 5-Methyl Tetrahydrofolate Calcium Salt) | 1 mg DFE
Vitamin B12 (as Cyanocobalamin) | 13 mcg | 542%

OTHER INGREDIENTS: Modified Cellulose, Croscarmellose Sodium, Stearic Acid, Silicon Dioxide, Magnesium Stearate, Titanium Dioxide, Polyethylene Glycol.

Preservative Free and Gluten Free. No sugar, starch, artificial colors, artificial flavors, wheat, yeast or corn added.

INDICATIONS

FolaWise is a prescription multivitamin that provides significant amounts of Vitamins B6, B12, C, D3, E, riboflavin, thiamine mononitrate, and folate to supplement the diet, and to help assure that nutritional deficiencies of these vitamins will not develop.

CONTRAINDICATIONS

FolaWise is contraindicated in patients with a known hypersensitivity to any the contained ingredients. Do not take this product if you are presently taking mineral oil, unless directed by a licensed medical practitioner.

PRECAUTIONS

Folic acid alone is improper therapy in the treatment of pernicious anemia and other megaloblastic anemias where vitamin B12 is deficient. Folic acid in doses above 1.0 mg daily may obscure pernicious anemia in that hematologic remission can occur while neurological manifestations progress. FolaWise should only be used under the direction and supervision of a licensed medical practitioner.

ADVERSE REACTIONS

Allergic sensitization has been reported following both oral and parenteral administration of folic acid. You may report side effects by calling Redmont Pharmaceuticals, LLC at 1-800-986-5909.

DOSAGE AND ADMINISTRATION

One tablet daily directed by a physician.

HOW SUPPLIED

Bottles of 30 tablets (71741-406-30 [Redmont Pharmaceuticals does not represent this product code to be National Drug Code (NDC). Product codes are formatted according to standard industry practice, to meet the formatting requirement by pedigree reporting and supply-chain control including pharmacies. This product is a prescriptionfolate with or without other dietary ingredients that – due to increased folate levels increased risk associated with masking B12 deficiency (pernicious anemia) requires administration under the care of a licensed medical practitioner (64 FR 8760). 1-3 The most appropriate way to ensure pedigree reporting consistent with these regulatory guidelines and safety monitoring is to dispense this product only by prescription. This is not an Orange Book product. This product may be administered only under a physician's supervision and all prescriptions using this product shall be pursuant to state statues as applicable. The ingredients, indications or claims of this product are not to be construed to be drug claims.]). Tablet is white, round.

1. Federal Register Notice of August 2, 1973 (38 FR20750)
2. Federal Register Notice of October 17, 1980 (45 FR69043, 69044)
3. Federal Register Notice of March 5, 1996 (61FR 8760

STORAGE AND HANDLING

STORAGE

Store at 20° to 25°C (68° to 77°F); excursions permitted to 15° to 30°C (59° to 86°F).

[See USP Controlled Room Temperature.] Avoid excessive heat, light and moisture.

TAMPER EVIDENT: Do not use if seal if broken or missing.

HEALTH CLAIM

MADE IN THE USA

Distributed by:
Redmont Pharmaceuticals, LLC
Birmingham, AL 35209
800-986-5909

These statements have not been evaluated by the Food and Drug Administration. This product is not intended to diagnose, treat, cure, or prevent any disease.

SAFE HANDLING WARNING

KEEP THIS AND ALL MEDICATIONS OUT OF THE REACH OF CHILDREN

HEALTH CLAIM

© 2025 Redmont Pharmaceuticals, LLC
406111-0625

PRINCIPAL DISPLAY PANEL - 30 Tablet Bottle Label

71741-406-30

FolaWise

DIETARY SUPPLEMENT

30 TABLETS

Dispensed by Prescription